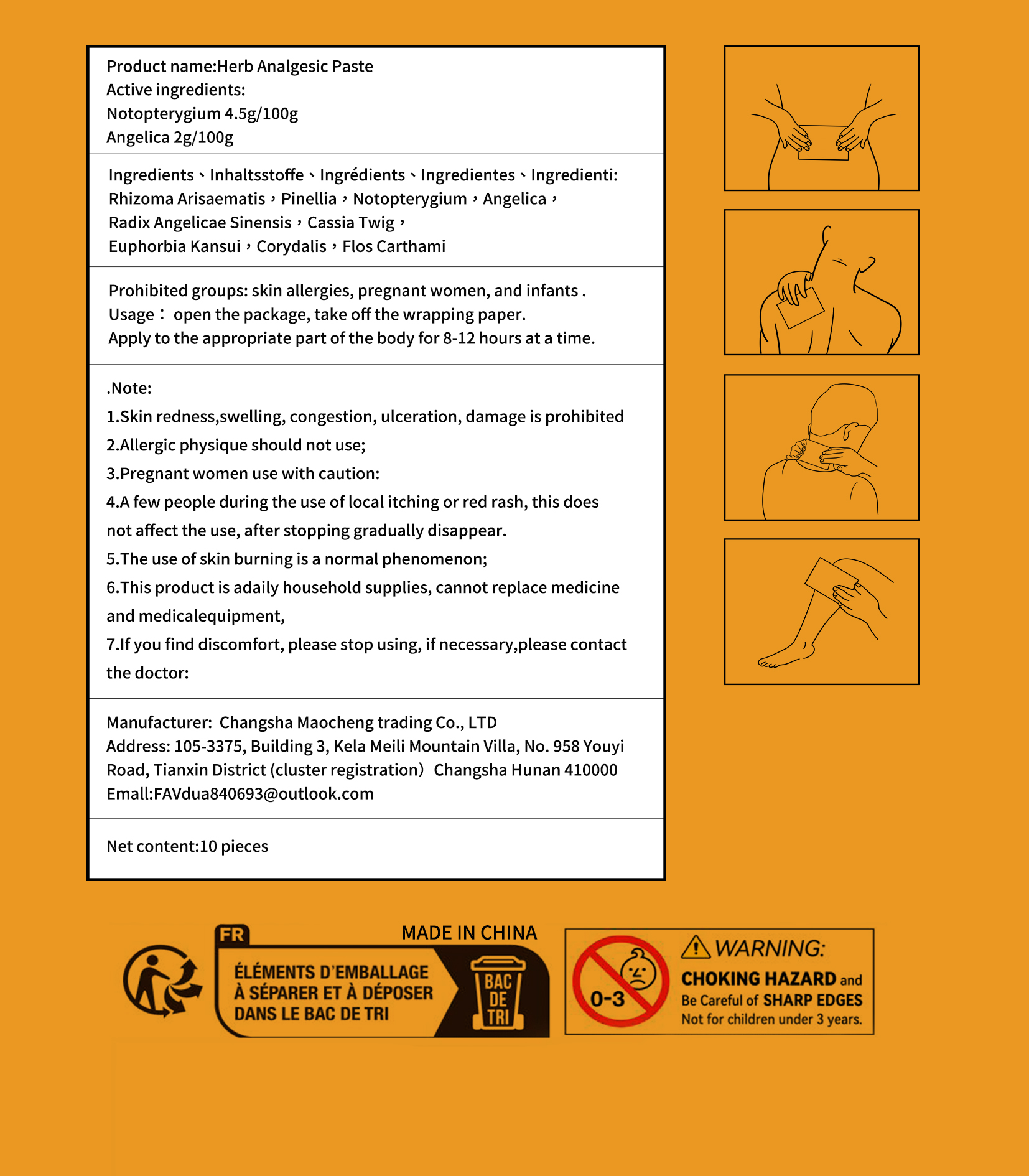 DRUG LABEL: Herb Analgesic
NDC: 84876-002 | Form: PASTE
Manufacturer: Changsha Maocheng Trading Co., Ltd
Category: otc | Type: HUMAN OTC DRUG LABEL
Date: 20250318

ACTIVE INGREDIENTS: INCISED NOTOPTERYGIUM RHIZOME OR ROOT (NOTOPTERYGIUM FRANCHETII) 4.5 g/100 g; ANGELICA SEED 2 g/100 g
INACTIVE INGREDIENTS: CORYDALIS SOLIDA WHOLE; CARTHAMUS TINCTORIUS (SAFFLOWER) FLOWER; CINNAMOMUM CASSIA TWIG; ARISAEMA TRIPHYLLUM ROOT; ANGELICA BISERRATA WHOLE; PINELLIA TERNATA ROOT; EUPHORBIA KANSUI WHOLE

Active ingredients:Notopterygium 4.5g/100gAngelica 2g/100g

INACTIVE INGREDIENT

Rhizoma Arisaematis（ARISAEMA TRIPHYLLUM ROOT） ,Pinellia ,Notopterygium , Angelica ,Radix Angelicae SinensisANGELICA BISERRATA , Cassia Twig ,Euphorbia Kansui , Corydalis , Flos Carthami

PURPOSE

relieve pain

WARNINGS

1.Skin redness,swelling, congestion, ulceration, damage is prohibited2.Allergic physique should not use;3.Pregnant women use with caution:4.A few people during the use of local itching or red rash, this doesnot affect the use, after stopping gradually disappear.5.The use of skin burning is a normal phenomenon;6.This product is adaily household supplies, cannot replace medicineand medicalequipment,

STOP USE

4.A few people during the use of local itching or red rash, this doesnot affect the use, after stopping gradually disappear.

DO NOT USE

1.Skin redness,swelling, congestion, ulceration, damage is prohibited2.Allergic physique should not use;3.Pregnant women use with caution:

keep out of reach ofchildren

INDICATIONS AND USAGE

Usage : open the package, take off the wrapping paper.
Apply to the appropriate part of the body for 8-12 hours at a time.

DOSAGE AND ADMINISTRATION

Apply to the appropriate part of the body for 8-12 hours at a time.

WHEN USING

When experiencing muscle soreness, one can use a hot pack to relieve the pain."